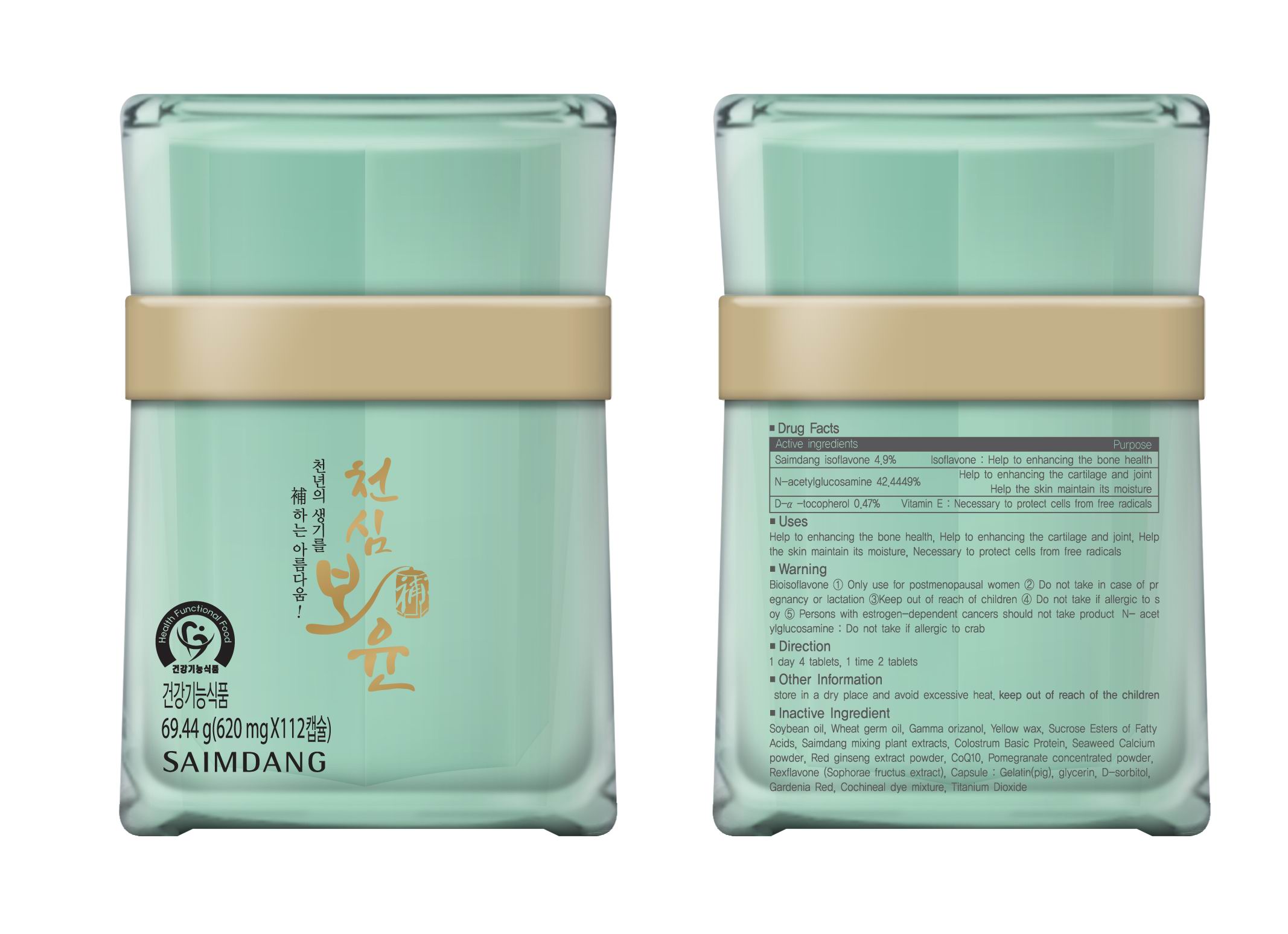 DRUG LABEL: Cheon Shim Bo Yun
NDC: 51220-4001 | Form: CAPSULE
Manufacturer: Saimdang Cosmetics Co., Ltd
Category: otc | Type: HUMAN OTC DRUG LABEL
Date: 20110406

ACTIVE INGREDIENTS: N-ACETYLGLUCOSAMINE 263 mg/1 1; .ALPHA.-TOCOPHEROL ACETATE, D- 3 mg/1 1; SOY ISOFLAVONES 30 mg/1 1
INACTIVE INGREDIENTS: SOYBEAN OIL; WHEAT GERM OIL; YELLOW WAX; CALCIUM; ASIAN GINSENG; POMEGRANATE; SOPHORA FLAVESCENS ROOT; GELATIN; GLYCERIN; SORBITOL; TITANIUM DIOXIDE; GARDENIA JASMINOIDES FRUIT; COCHINEAL

Drug Facts

Active ingredient: Isoflavone, N-acetylglucosamine, D-alpha tocopherol

Inactive ingredient: soybean oil, wheat germ oil, gamma orizanol, yellow wax, sucrose esters of fatty acids, colostrum basic protein, seaweed clacium powder, red ginseng extract powder, CoQ10, pomegranate concentrated powder, sophorae fructus extract, gelatin, D-sorbitol, gardenia red, cochineal dye mixture, titanium dioxide

DOSAGE AND ADMINISTRATION

1 day 4 tablets, 1 time 2 tablets

INDICATIONS AND USAGE

only use for postmenopausal women

Keep outof reach of children

PURPOSE

helps enhancing the bone health

WARNINGS

■ Bioisoflavone ① Only use for postmenopausal women ② Do not take in case of pregnancy or lactation ③Keep out of reach of children ④ Do not take if allergic to soy ⑤ Persons with estrogen-dependent cancers should not take product
■ N- acetylglucosamine : Do not take if allergic to crab